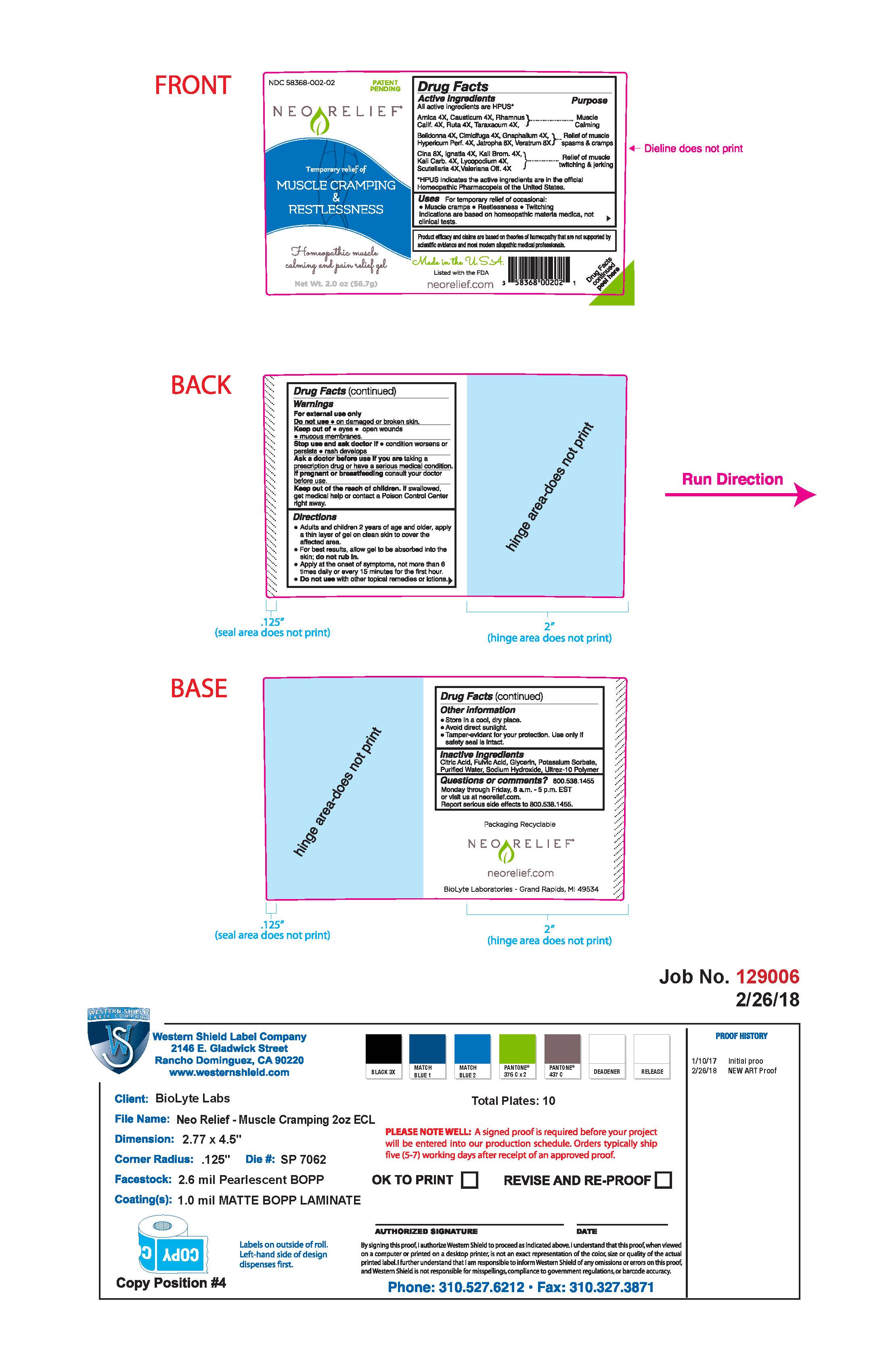 DRUG LABEL: NEORELIEF FOR MUSCLE CRAMPLING AND RESTLESSNESS
NDC: 58368-002 | Form: GEL
Manufacturer: BioLyte Laboratories, LLC
Category: homeopathic | Type: HUMAN OTC DRUG LABEL
Date: 20260127

ACTIVE INGREDIENTS: CAUSTICUM 4 [hp_X]/1 g; JATROPHA CURCAS SEED 8 [hp_X]/1 g; FRANGULA CALIFORNICA BARK 4 [hp_X]/1 g; RUTA GRAVEOLENS FLOWERING TOP 4 [hp_X]/1 g; ARNICA MONTANA 4 [hp_X]/1 g; ATROPA BELLADONNA ROOT 4 [hp_X]/1 g; BLACK COHOSH 4 [hp_X]/1 g; ARTEMISIA CINA PRE-FLOWERING TOP 8 [hp_X]/1 g; PSEUDOGNAPHALIUM OBTUSIFOLIUM 4 [hp_X]/1 g; HYPERICUM PERFORATUM 4 [hp_X]/1 g; STRYCHNOS IGNATII SEED 4 [hp_X]/1 g; POTASSIUM BROMIDE 4 [hp_X]/1 g; POTASSIUM CARBONATE 4 [hp_X]/1 g; LYCOPODIUM CLAVATUM SPORE 4 [hp_X]/1 g; SCUTELLARIA LATERIFLORA 4 [hp_X]/1 g; TARAXACUM OFFICINALE 4 [hp_X]/1 g; VALERIAN 8 [hp_X]/1 g; VERATRUM ALBUM ROOT 8 [hp_X]/1 g
INACTIVE INGREDIENTS: CITRIC ACID MONOHYDRATE; FULVIC ACID; POTASSIUM SORBATE; WATER; SODIUM HYDROXIDE; GLYCERIN; CARBOMER HOMOPOLYMER TYPE C

Drug Facts Active Ingredients

All active ingredients are HPUS*

Arncia 4X, Causticum 4X, Rhamnus Calif. 4X, Ruta 4X, Taraxacum 4X,

Belladonna 4X, Cimicifuga 4X, Gnaphalium 4X, Hypericum Perf. 4X, Jatropha 8X, Veratrum 8X

Cina 8X, Ignatia 4X, Kali Brom. 4X, Kali Carb. 4X, Lycopodium 4X, Scutellaria 4X, Valeriana Off. 4X

*HPUS indicates the active ingredients are in the official Homeopathic Pharmacopeia of the United States.

Purpose

For the temporary relief of occasional:

Muscle cramps, restlessness, twiching

Indications are based on homeopathic materia medica, not clinical tests.

Uses

For temporary relief of occasional muscle cramps, restlessness and twitching

Warnings

For external use only

Do not use on damaged or broken skin.

Keep out of eyes, open wounds, mucous membranes

Warnings

Stop use and ask doctor if condition worsens or persists, rash develops

Warnings

Ask a doctor before use if you are taking a prescription drug or have a serious medical condition.

Warnings

If pregnant or breast-feeding, consult your doctor before use.

Warnings

Keep out of the reach of children. If swallowed, get medical help or contact a Poison Control Center right away.

Directions

Adults and children 2 years of age and older, apply a thin layer of gel on clean skin to cover the affected area.

For best results, allow gel to be absorbed into the skin; do not rub in.

Apply at the onset of symptoms, not more than 6 times daily or every 15 minutes for the first hour.

Do not use with other topical remedies or lotions.

Other Information

Store in a cool, dry place

Avoid direct sunlight

Tamper-evident for your protection. Use only if safety seal is intact.

Inactive Ingredients

Citric Acid, Fulvic acid, Glycerin, Potassium Sorbate, Purified Water, Sodium Hydroxide, Ultrez-10 Polymer

Questions or comments?

800.538.1455

Monday through Friday 8 a.m. - 5 p.m. EST or visit us at neorelief.com

Report serious side effects to 800.538.1455

Additional Label Content

Required FTC Disclosure: Product efficacy and claims are based on theories of homeopathy that are not supported by scientific evidence and most modern allopathic medical professionals.

Made in the USA

Listed with the FDA

(UPC code: 3 58368 00202 1)

Drug Facts continued peel here

Packaging Recyclable

neorelief.com

BioLyte Laboratories- Grand Rapids, MI 49534

NEORELIEF for Muscle Cramping and Restlessness 56.7 g Bottle

NDC 58368-002-02 Patent pending

NeoRelief

Temporary relief of muscle cramping and restlessness

Homeopathic muscle calming and pain relief gel

Net Wt. 2.0 oz (56.7g)